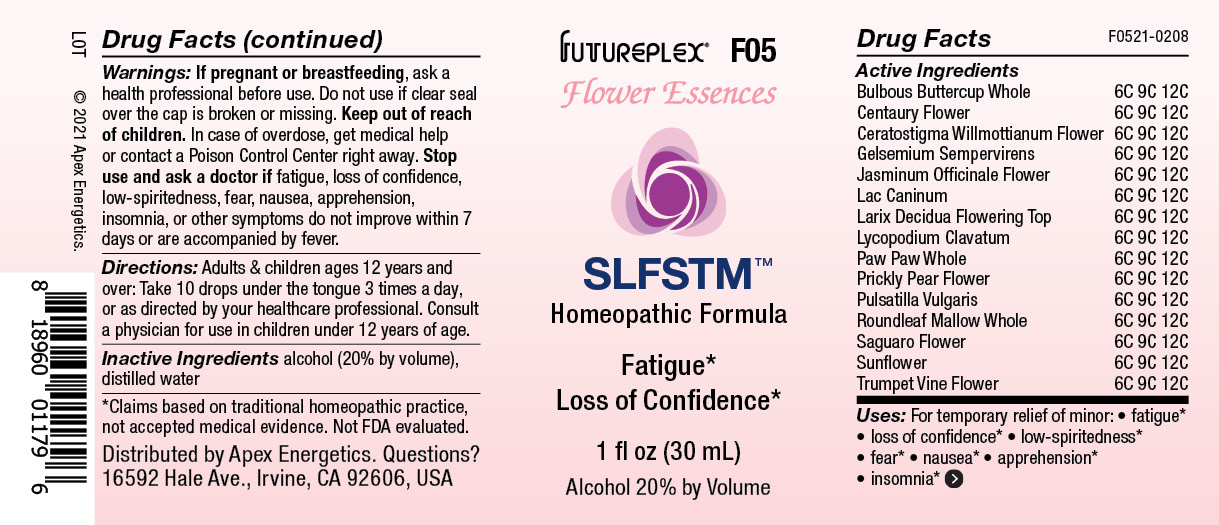 DRUG LABEL: F05
NDC: 63479-0605 | Form: SOLUTION/ DROPS
Manufacturer: Apex Energetics Inc.
Category: homeopathic | Type: HUMAN OTC DRUG LABEL
Date: 20240108

ACTIVE INGREDIENTS: LYCOPODIUM CLAVATUM SPORE 12 [hp_C]/1 mL; ASIMINA TRILOBA WHOLE 12 [hp_C]/1 mL; CARNEGIEA GIGANTEA FLOWER 12 [hp_C]/1 mL; HELIANTHUS ANNUUS FLOWERING TOP 12 [hp_C]/1 mL; CENTAURIUM ERYTHRAEA FLOWER 12 [hp_C]/1 mL; OPUNTIA FICUS-INDICA FLOWER 12 [hp_C]/1 mL; PULSATILLA VULGARIS WHOLE 12 [hp_C]/1 mL; CAMPSIS RADICANS FLOWER 12 [hp_C]/1 mL; MALVA NEGLECTA WHOLE 12 [hp_C]/1 mL; JASMINUM OFFICINALE FLOWER 12 [hp_C]/1 mL; RANUNCULUS BULBOSUS 12 [hp_C]/1 mL; CERATOSTIGMA WILLMOTTIANUM FLOWER 12 [hp_C]/1 mL; GELSEMIUM SEMPERVIRENS ROOT 12 [hp_C]/1 mL; CANIS LUPUS FAMILIARIS MILK 12 [hp_C]/1 mL; LARIX DECIDUA FLOWERING TOP 12 [hp_C]/1 mL
INACTIVE INGREDIENTS: ALCOHOL; WATER

F05

Active Ingredients
Bulbous Buttercup Whole | 6C 9C 12C
Centaury Flower | 6C 9C 12C
Ceratostigma Willmottianum Flower | 6C 9C 12C
Gelsemium Sempervirens | 6C 9C 12C
Jasminum Officinale Flower | 6C 9C 12C
Lac Caninum | 6C 9C 12C
Larix Decidua Flowering Top | 6C 9C 12C
Lycopodium Clavatum | 6C 9C 12C
Paw Paw Whole | 6C 9C 12C
Prickly Pear Flower | 6C 9C 12C
Pulsatilla Vulgaris | 6C 9C 12C
Roundleaf Mallow Whole | 6C 9C 12C
Saguaro Flower | 6C 9C 12C
Sunflower | 6C 9C 12C
Trumpet Vine Flower | 6C 9C 12C

INDICATIONS AND USAGE

Uses:

For temporary relief of minor:

fatigue*

loss of confidence*

low-spiritedness*

fear*

nausea*

apprehension*

insomnia*

*Claims based on traditional homeopathic practice, not accepted medical evidence. Not FDA evaluated.

Warnings:

PREGNANCY OR BREAST FEEDING

If pregnant or breastfeeding, ask a health professional before use.

Do not use if clear seal over the cap is broken or missing.

Keep out of reach of children. In case of overdose, get medical help or contact a Poison Control Center right away.

Stop use and ask a doctor if fatigue, loss of confidence, low-spiritedness, fear, nausea, apprehension, insomnia, or other symptoms do not improve within 7 days or are accompanied by fever.

Directions:

Adults & children ages 12 years and over: Take 10 drops under the tongue 3 times a day, or as directed by your healthcare professional. Consult a physician for use in children under 12 years of age.

Inactive Ingredients

alcohol (20% by volume), distilled water

Distributed by Apex Energetics. Questions?

16592 Hale Ave., Irvine, CA 92606, USA

PACKAGE LABEL

FUTUREPLEX® F05

Flower Essences

SLFSTM™

Homeopathic Formula

Fatigue*

Loss of Confidence*

1 fl oz (30 mL)

Alcohol 20% by Volume